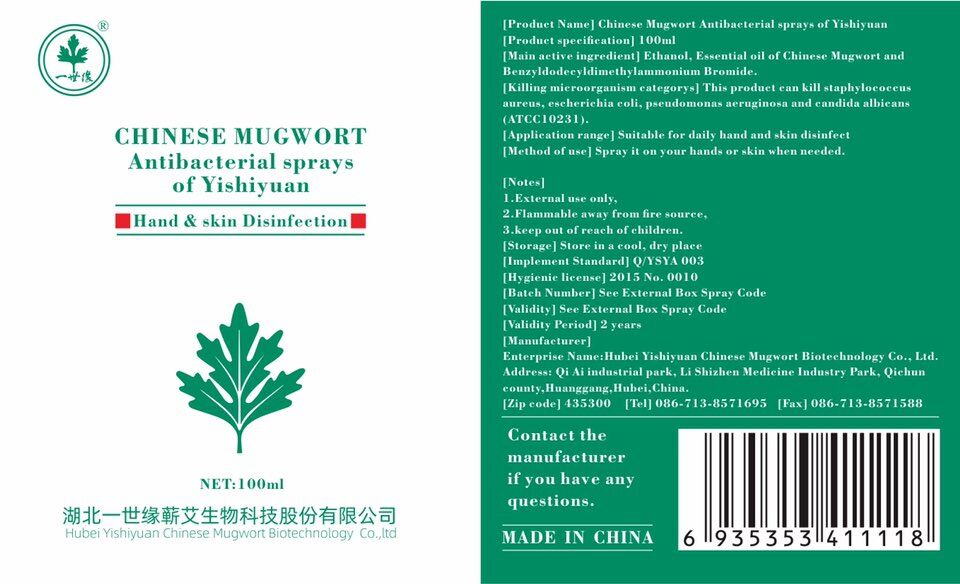 DRUG LABEL: Chinese Mugwort Antibacterial Sprays of Yishiyuan
NDC: 75507-1011 | Form: LIQUID
Manufacturer: Hubei Yishiyuan Chinese Mugwort Biotechnology Co., Ltd.
Category: otc | Type: HUMAN OTC DRUG LABEL
Date: 20200424

ACTIVE INGREDIENTS: ALCOHOL 75 mL/100 mL
INACTIVE INGREDIENTS: ARTEMISIA ARGYI LEAF; BENZODODECINIUM BROMIDE; WATER

YiShiYuan, Chinese Mugwort Antibacterial Sprays, Liquid, 100mL

Active Ingredient(s)

Alcohol 75% v/v. Purpose: Antiseptic.

Kill staphylococcus aureus, escherichia coli, pseudomonas aeruginosa, and candida albicans (ATCC10231).

Purpose

Antiseptic, Hand Sanitizer

Use

Hand Sanitizer to help reduce bacteria that potentially can cause disease. For use when soap and water are not available.

Suitable for daily hand and skin disinfection.

Warnings

1. External use only.

2. Flammable, away from fire source.

3. Keep out of reach of children.

Do not use

- on children less than 2 months of age
- on open skin wounds
- in the eyes. in case of contact, rinse eyes thoroughly with water

When using this product keep out of eyes, ears, and mouth.

In case of contact with eyes, rinse eyes thoroughly with water.

Stop use and ask a doctor if irritation and redness develop and persist for more than 72 hours.

Keep out of reach of children. If swallowed, get medical help or contact a Poison Control Center right away.

Directions

Spray on your hands or skin when needed.

Other information

Store in a cool, dry place.

Inactive ingredients

Water, Essential Oil of Chinese Mugwort, Benzyldodecyldimethylammonium Bromide.